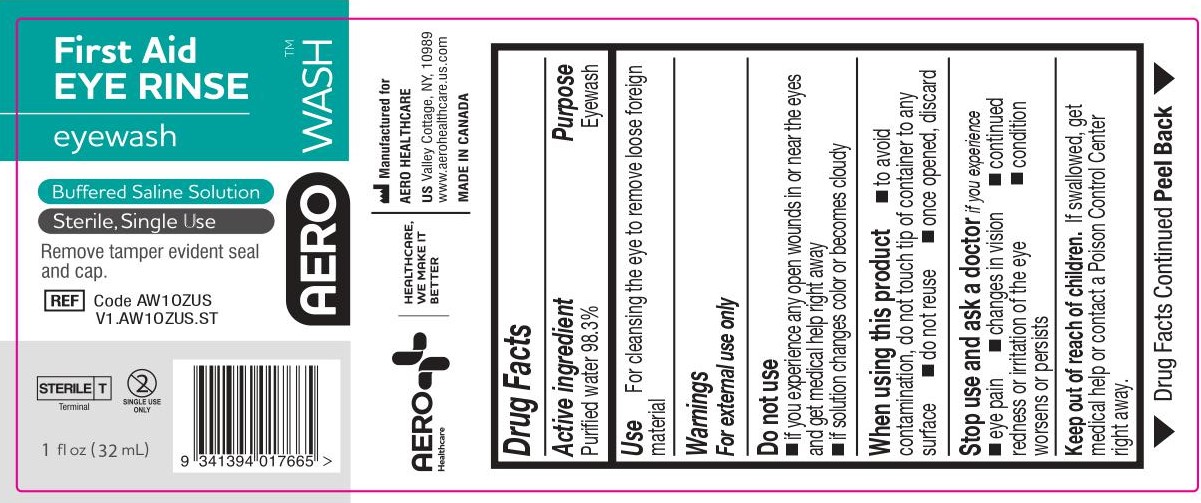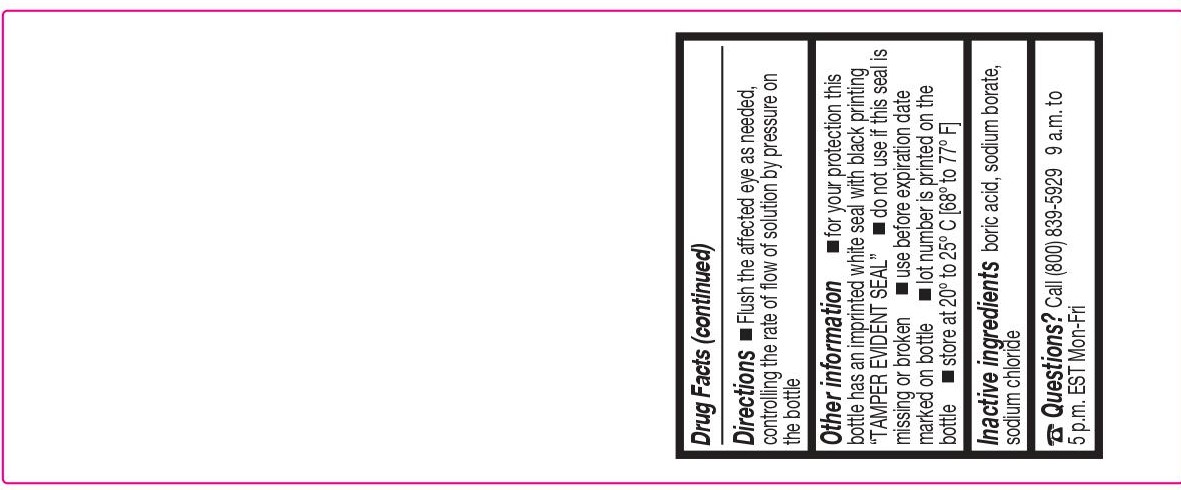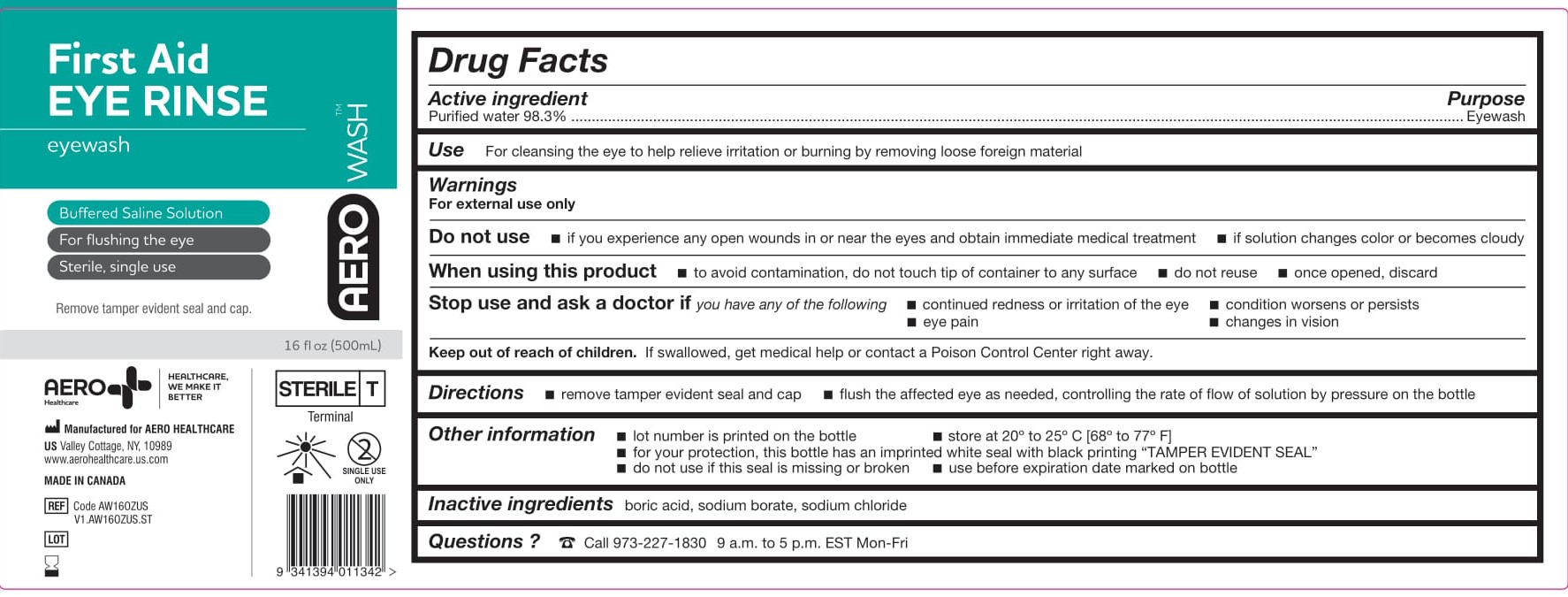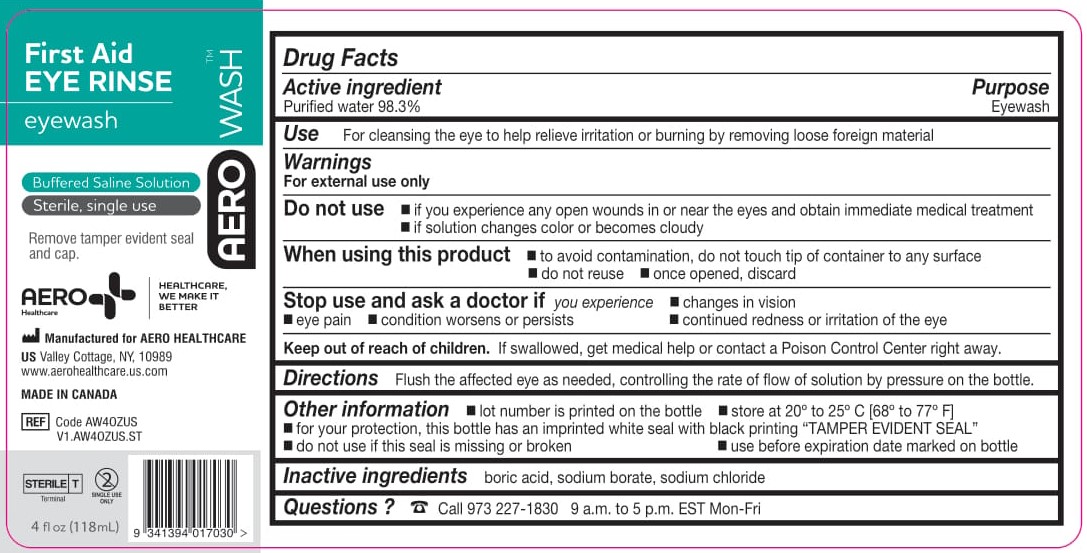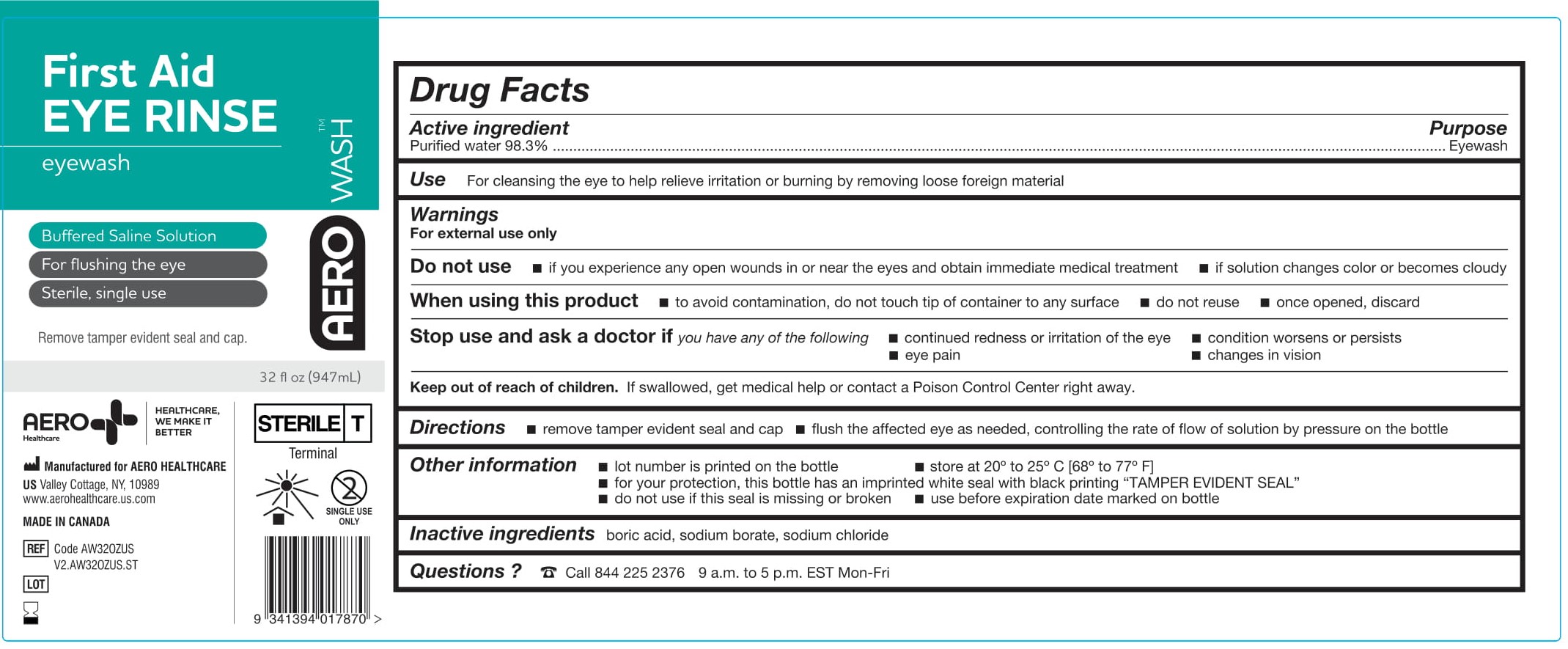 DRUG LABEL: AeroWash Eyewash
NDC: 55305-115 | Form: LIQUID
Manufacturer: Aero Healthcare US LLC
Category: otc | Type: HUMAN OTC DRUG LABEL
Date: 20250226

ACTIVE INGREDIENTS: WATER 0.983 mL/1 mL
INACTIVE INGREDIENTS: BORIC ACID; SODIUM CHLORIDE; SODIUM BORATE

AeroWash Eyewash - eyewash solution

ACTIVE INGREDIENT

Purified water 98.3%

PURPOSE

Eyewash

WARNINGS

For external use only

Do not use

- if you experience any open wounds in or near the eyes and obtain immediate medical treatment
- if solution changes color or becomes cloudy

When using this product

- to avoid contamination, do not touch tip of container to any surface
- do not reuse
- once opened, discard

Stop use and ask a doctor if you have any of the following

- changes in vision
- eye pain
- condition worsens or persists
- continued redness or irritation of the eye

Use

For cleansing the eye to help relieve irritation or burning by removing loose foreign material

KEEP OUT OF REACH OF CHILDREN

If swallowed, get medical help or contact a Poison Control Center right away.

DIRECTIONS

Flush the affected eye as needed, controlling the rate of flow of solution by pressure on the bottle.

OTHER INFORMATION

- lot number is printed on the bottle
- store at 20° to 25° C [68° to 77° F)
- for your protection, this bottle has an imprinted white seal with black printing “TAMPER EVIDENT SEAL”
- do not use if this seal is missing or broken
- use before expiration date marked on bottle

INACTIVE INGREDIENTS

boric acid, sodium borate, sodium chloride